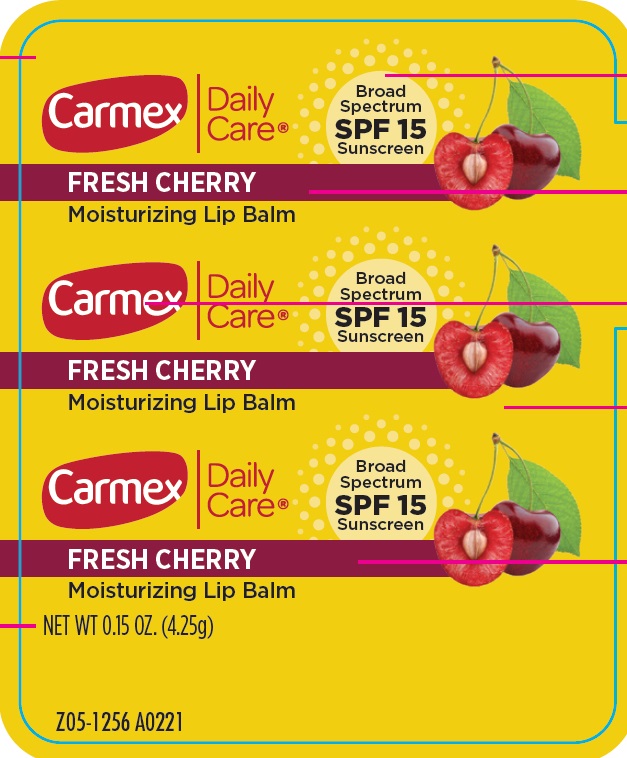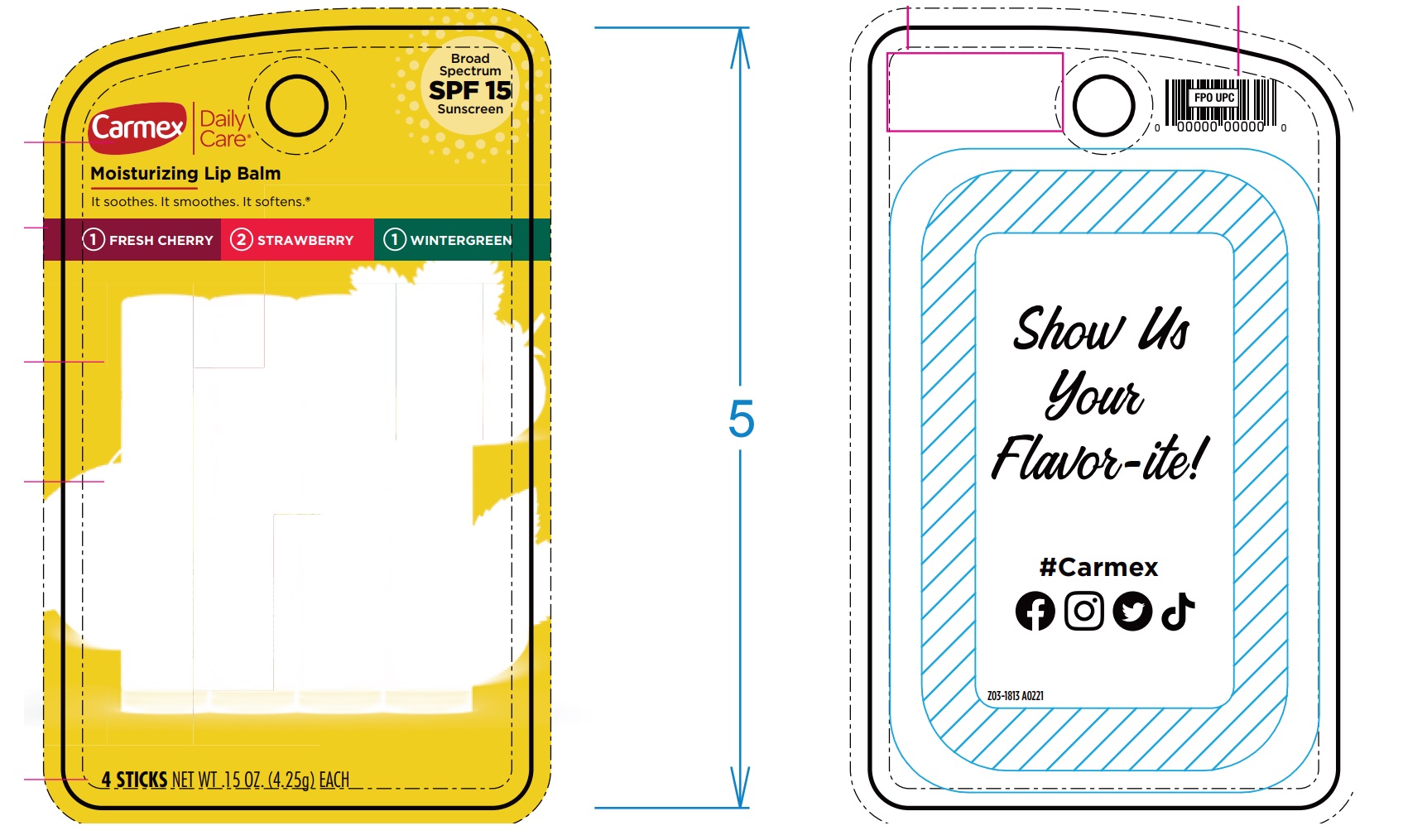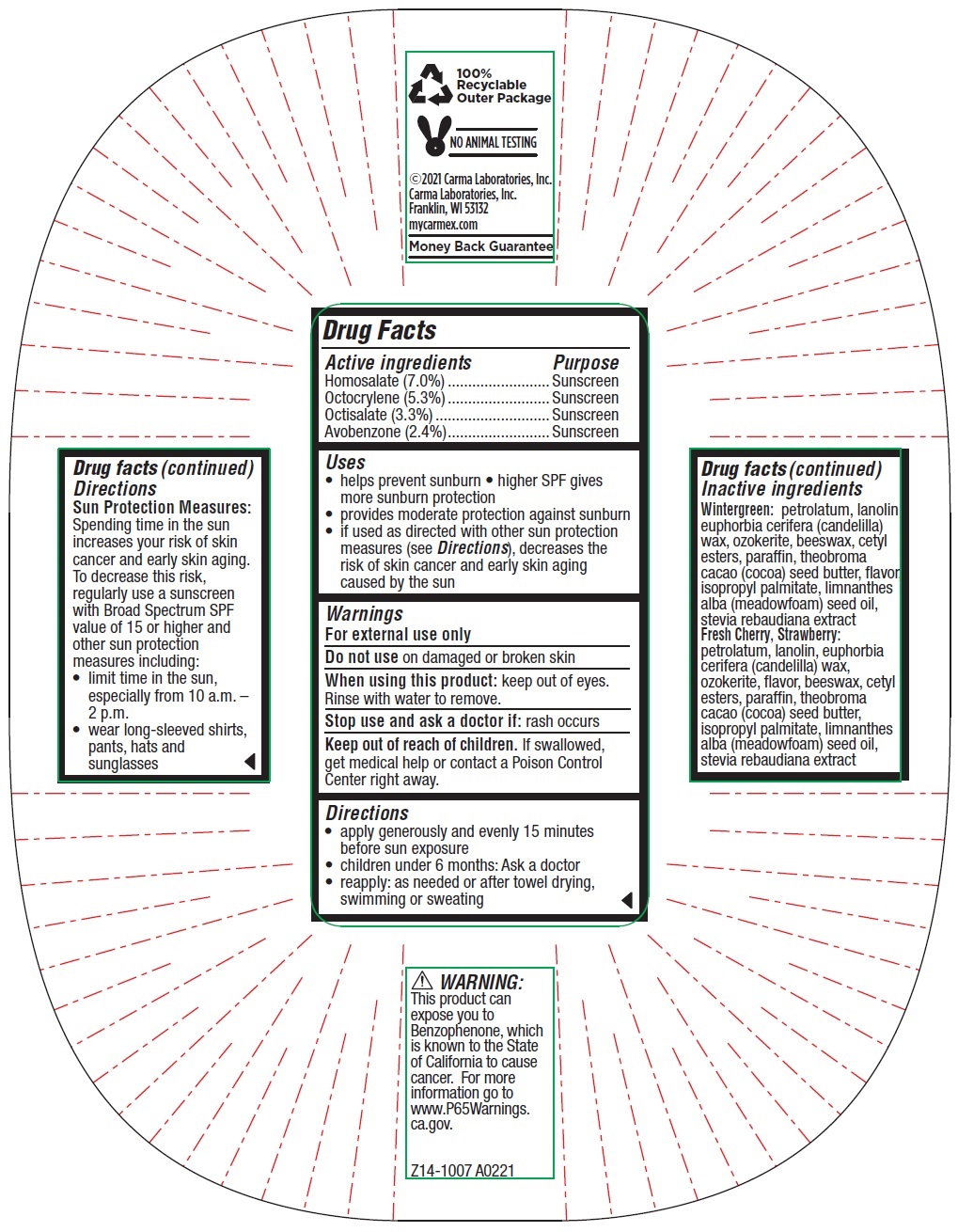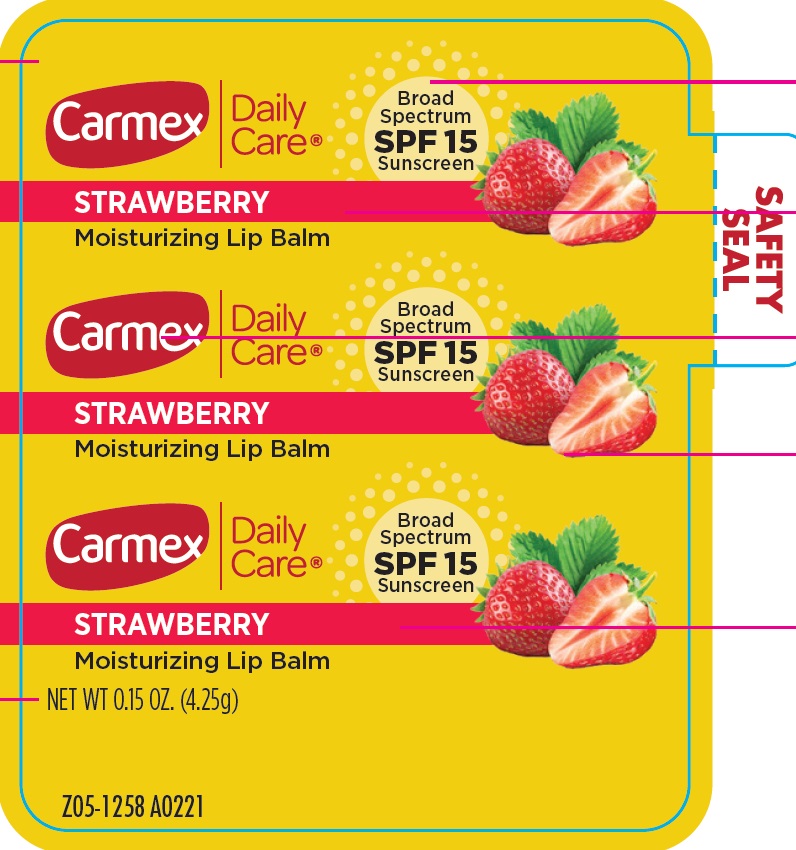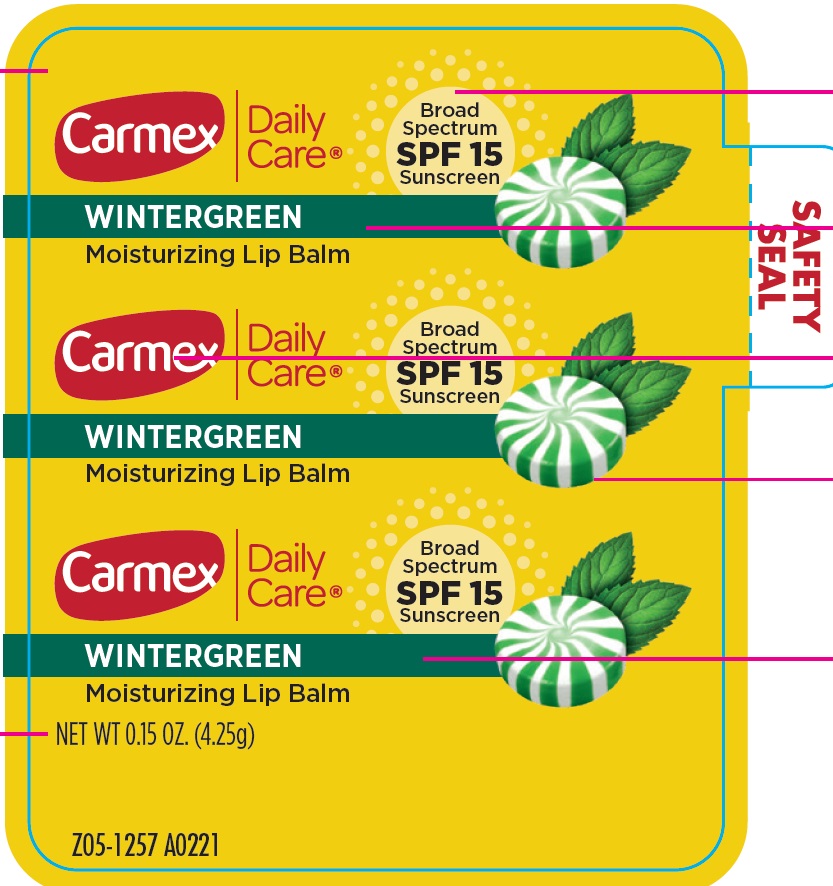 DRUG LABEL: Carmex Daily Care Moisturizing Lip SPF 15 Assorted
NDC: 10210-0078 | Form: KIT | Route: TOPICAL
Manufacturer: Carma Laboratories, Inc.
Category: otc | Type: HUMAN OTC DRUG LABEL
Date: 20240405

ACTIVE INGREDIENTS: HOMOSALATE 70 mg/1 g; OCTOCRYLENE 53 mg/1 g; OCTISALATE 33 mg/1 g; AVOBENZONE 24 mg/1 g; HOMOSALATE 70 mg/1 g; OCTOCRYLENE 53 mg/1 g; OCTISALATE 33 mg/1 g; AVOBENZONE 24 mg/1 g; HOMOSALATE 70 mg/1 g; OCTOCRYLENE 53 mg/1 g; OCTISALATE 33 mg/1 g; AVOBENZONE 24 mg/1 g
INACTIVE INGREDIENTS: PETROLATUM; LANOLIN; CANDELILLA WAX; YELLOW WAX; CETYL ESTERS WAX; PARAFFIN; COCOA BUTTER; ISOPROPYL PALMITATE; MEADOWFOAM SEED OIL; PETROLATUM; LANOLIN; CANDELILLA WAX; YELLOW WAX; CETYL ESTERS WAX; PARAFFIN; COCOA BUTTER; ISOPROPYL PALMITATE; MEADOWFOAM SEED OIL; PETROLATUM; LANOLIN; CANDELILLA WAX; YELLOW WAX; CETYL ESTERS WAX; PARAFFIN; COCOA BUTTER; ISOPROPYL PALMITATE; MEADOWFOAM SEED OIL

Carmex Daily Care Moisturizing Lip Balm SPF 15 STICK Assorted,1 Fresh Cherry + 2 Strawberry + 1 Wintergreen

Active ingredients

Homosalate (7.0%)

Octocrylene (5.3%)

Octisalate (3.3%)

Avobenzone (2.4%)

Purpose

Sunscreen

Uses

- helps prevent sunburn
- higher SPF gives more sunburn protection
- provides moderate protection against sunburn
- if used as directed with other sun protection measures (see Directions), decreases the risk of skin cancer and early skin aging caused by the sun

Warnings

For external use only

Do not use

on damaged or broken skin

When using this product:

keep out of eyes. Rinse with water to remove.

Stop use and ask a doctor if:

rash occurs

Keep out of reach of children.

If swallowed, get medical help or contact a Posion Control Center right away.

Directions

- apply generously and evenly 15 minutes before sun exposure
- children under 6 months: Ask a doctor
- reapply: as needed ot after towel drying, swimming or sweating

Sun Protection Measures:Spending time in the sun increases your risk of skin cancer and early skin aging. To decrease this risk, regularly use a sunscreen SPF value of 15 or higher and other sun protection measures including:

- limit time in the sun, especially from 10 a.m. - 2 p.m.
- wear long-sleeved shirts, pants, hats and sunglasses

Inactve ingredients

Wintergreen:petrolatum, lanolin, euphorbia cerifera (candelilla) wax, ozokerite, beeswax, cetyl esters, paraffin, theobroma cacao (cocoa) seed butter, flavor, isopropyl palmitate, limnanthes alba (meadowfoam) seed oil, stevia rebaudiana extract

Fresh Cherry, Strawberry:petrolatum, lanolin, euphorbia cerifera (candelilla) wax, ozokerite, flavor, beeswax, cetyl esters, paraffin, theobroma cacao (cocoa) seed butter, isopropyl palmitate, limnanthes alba (meadowfoam) seed oil, stevia rebaudiana extract